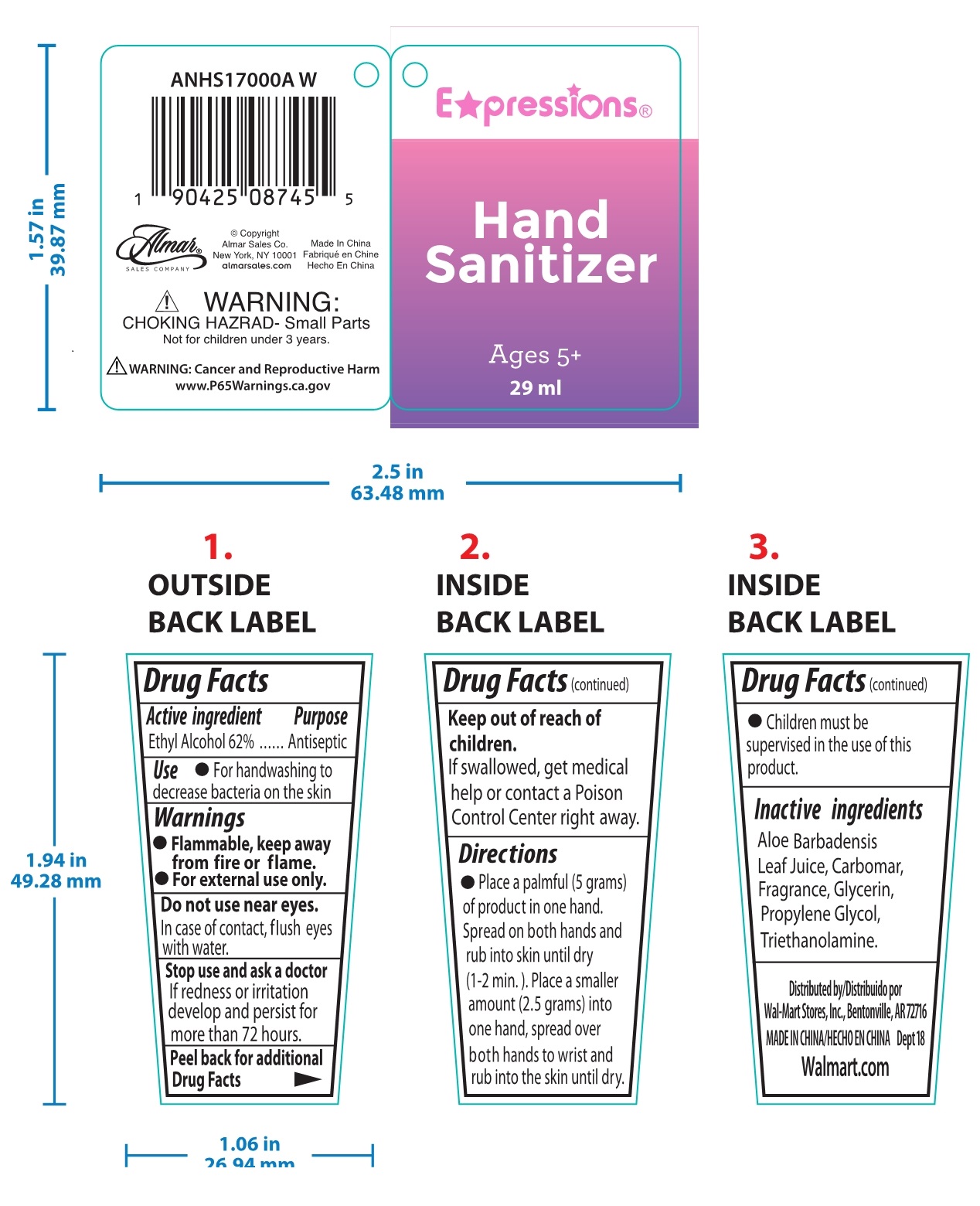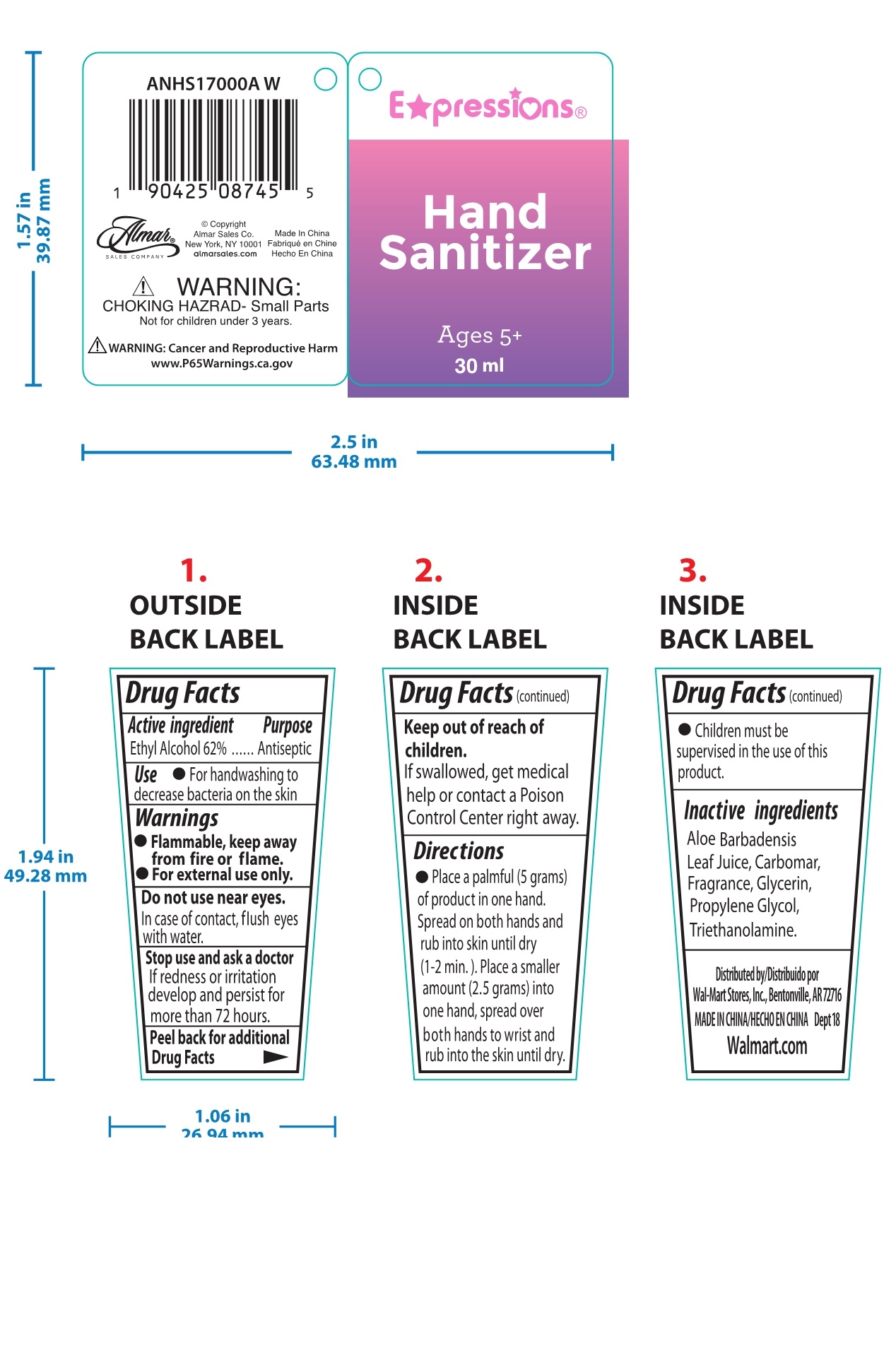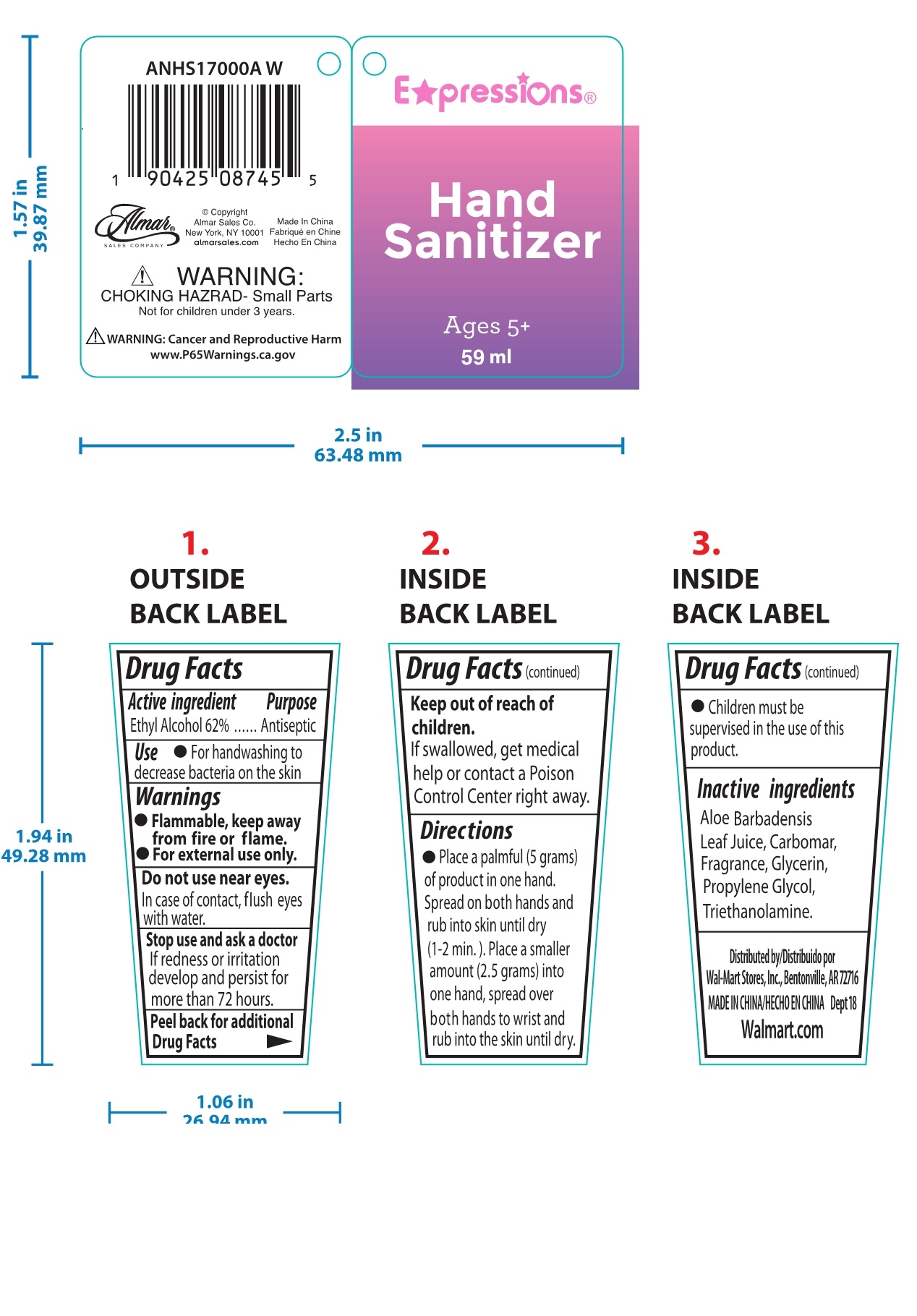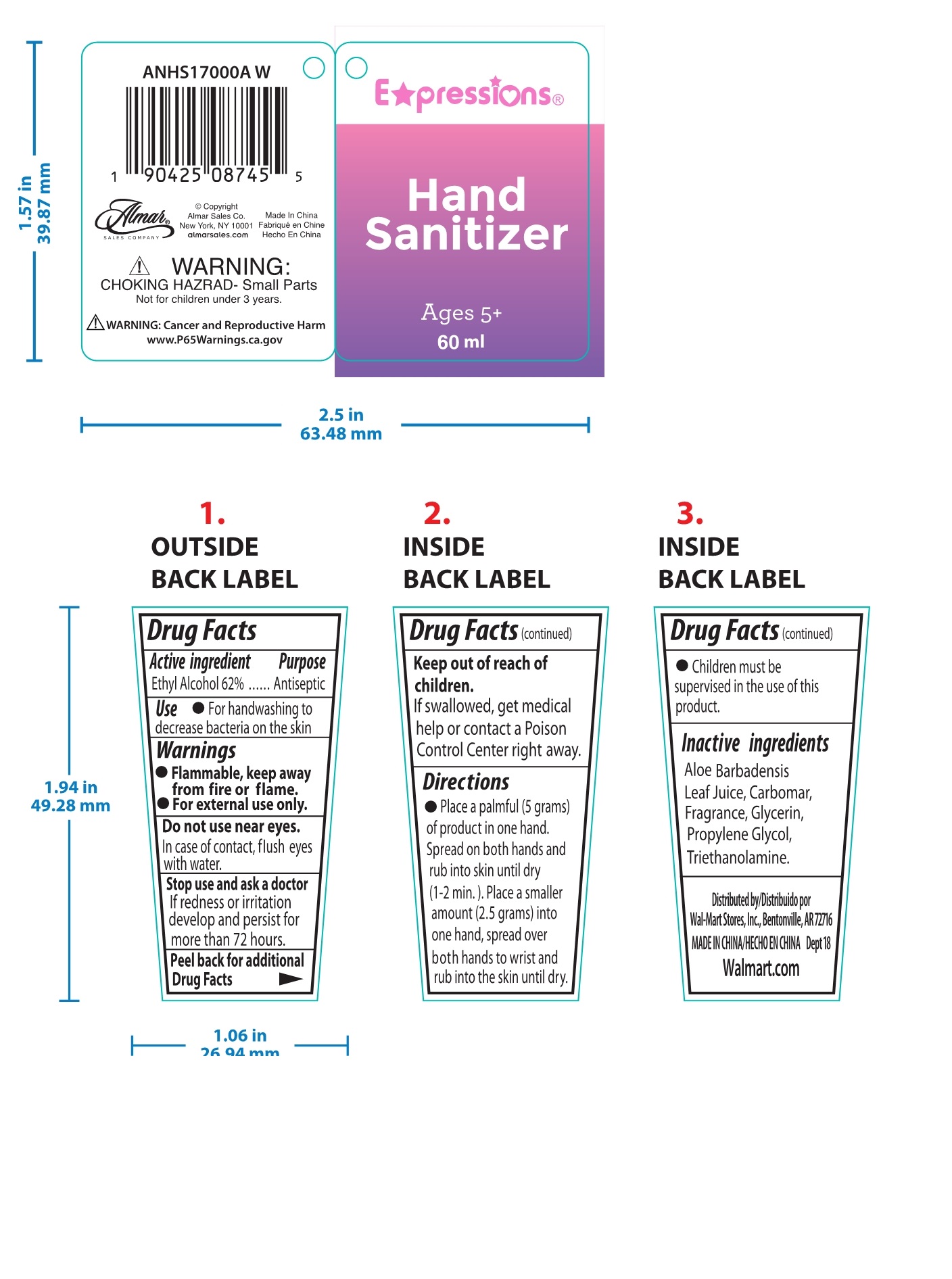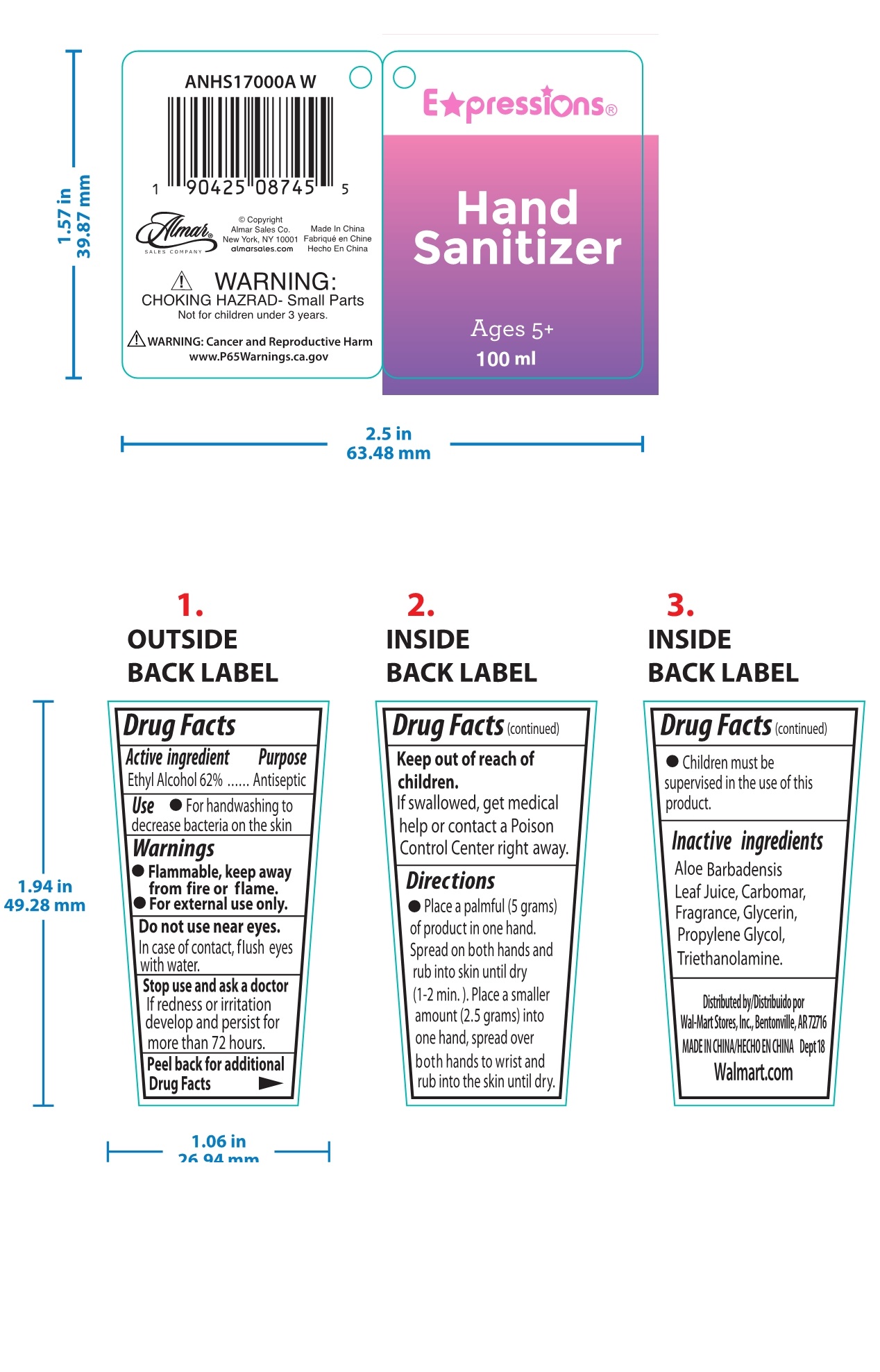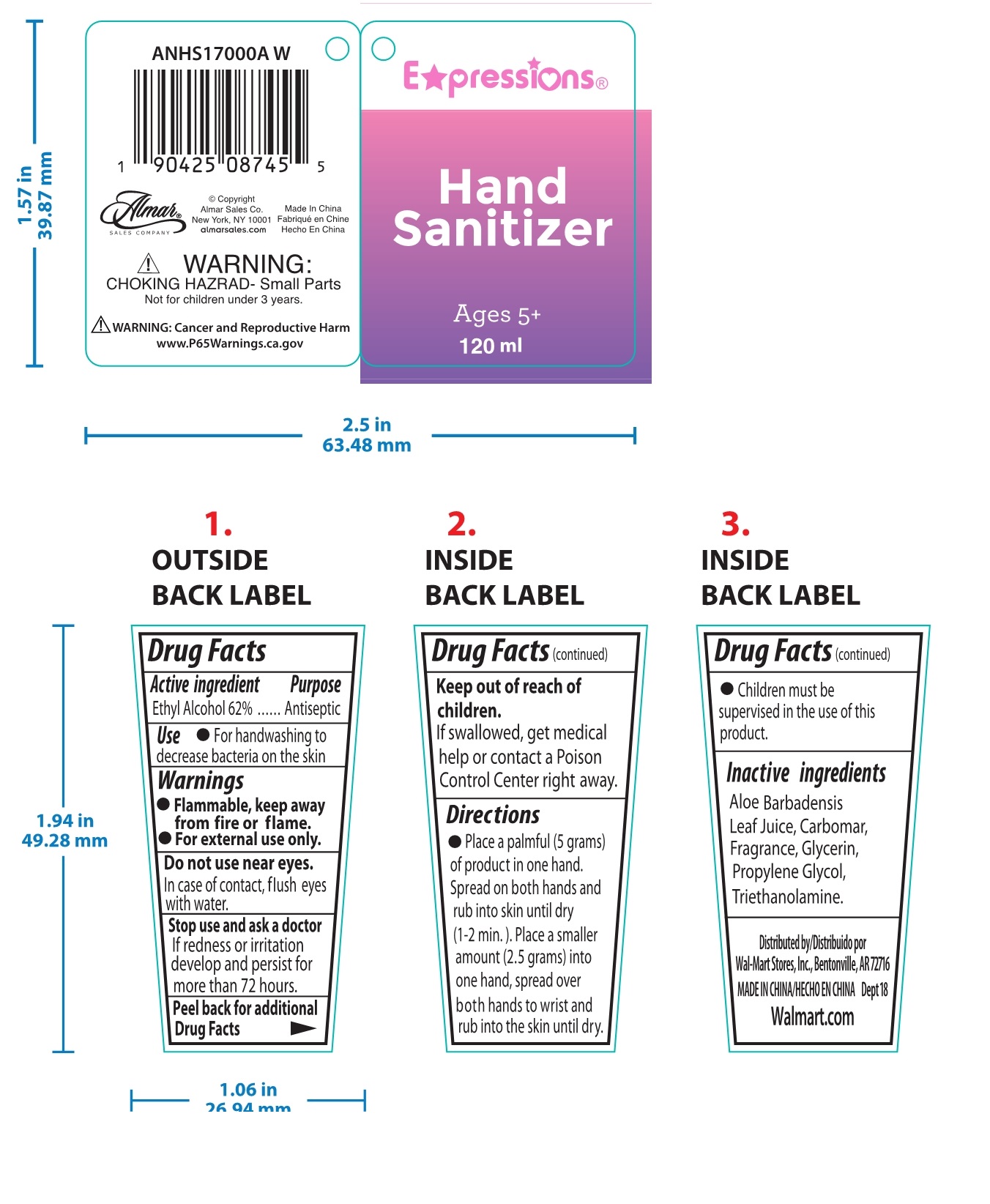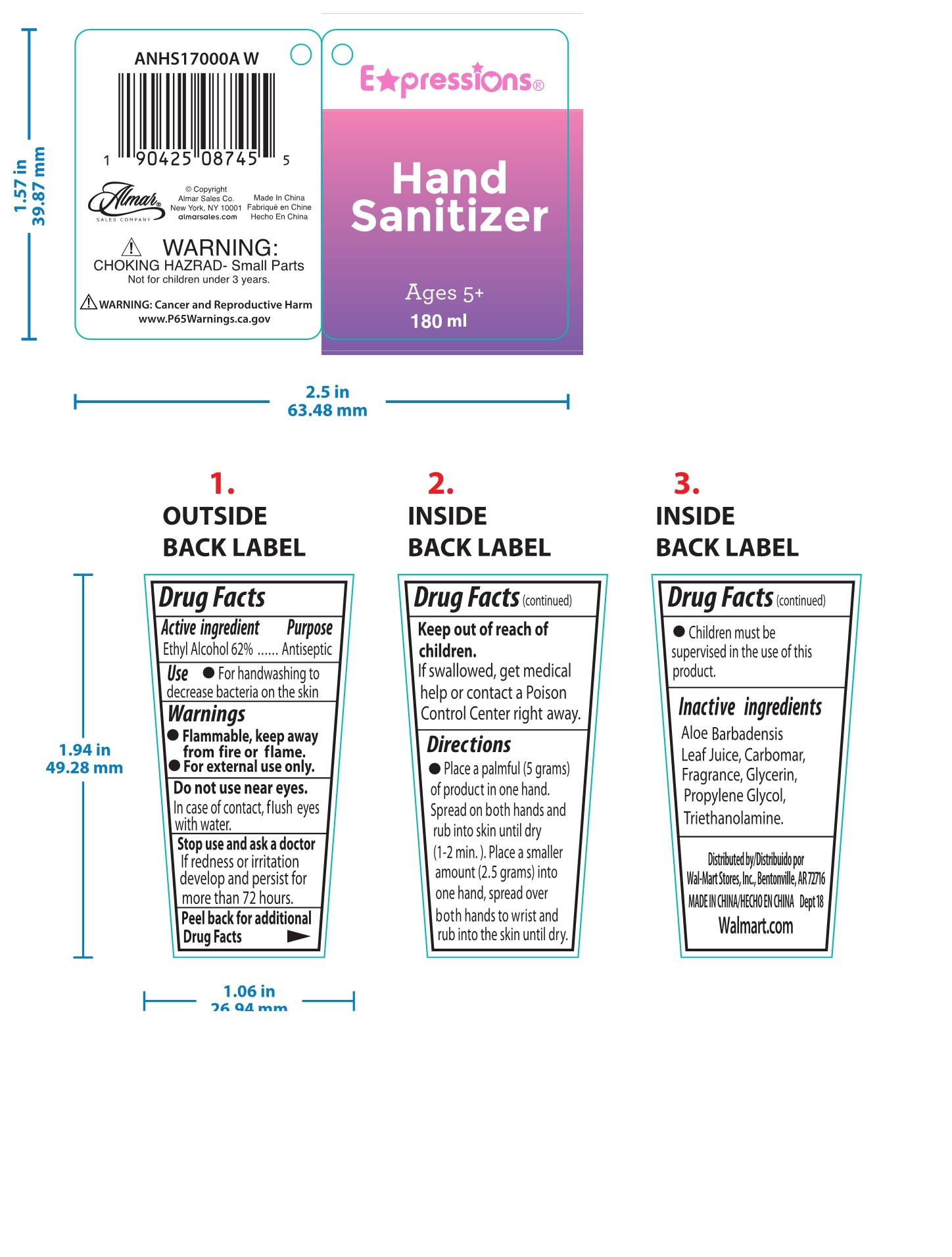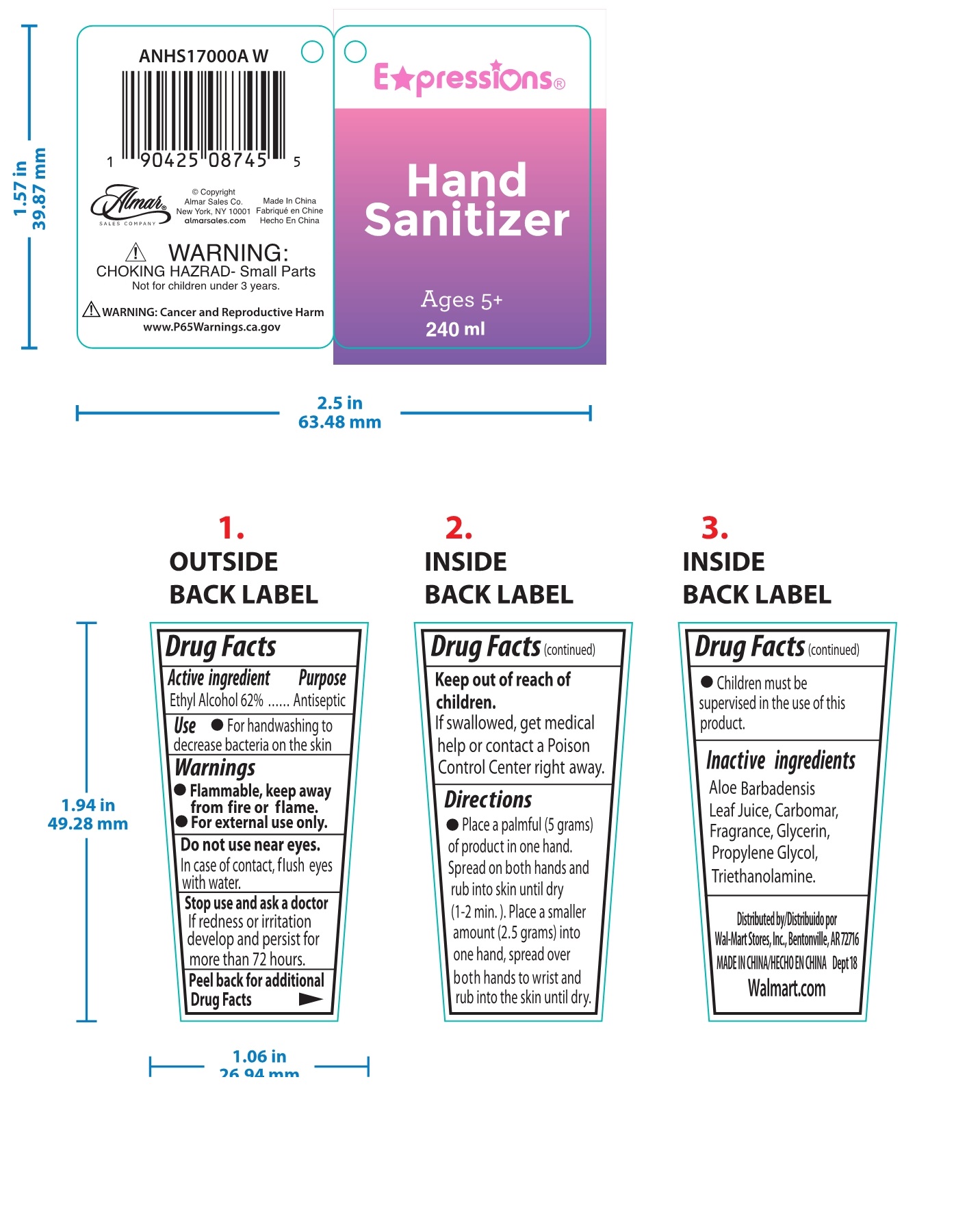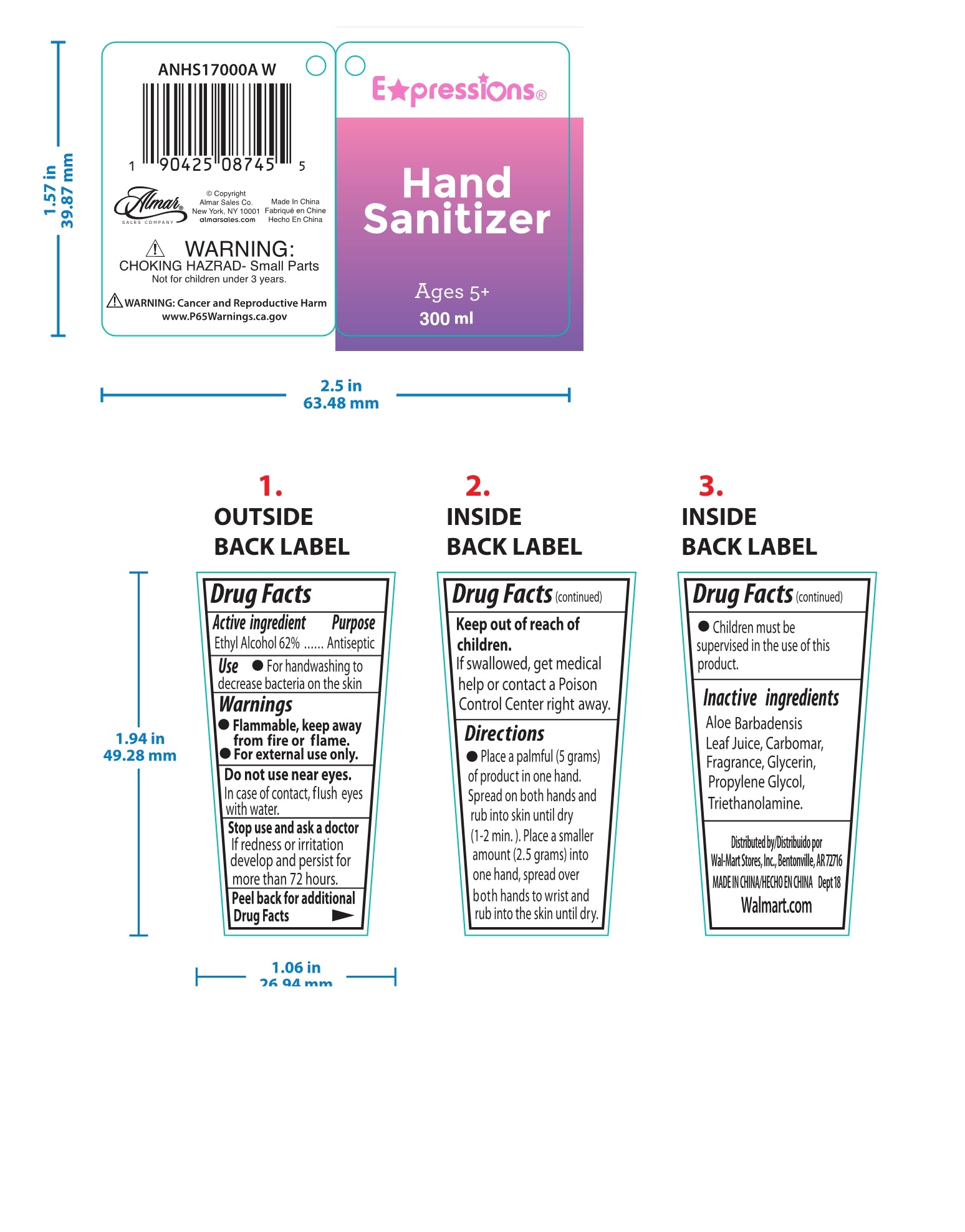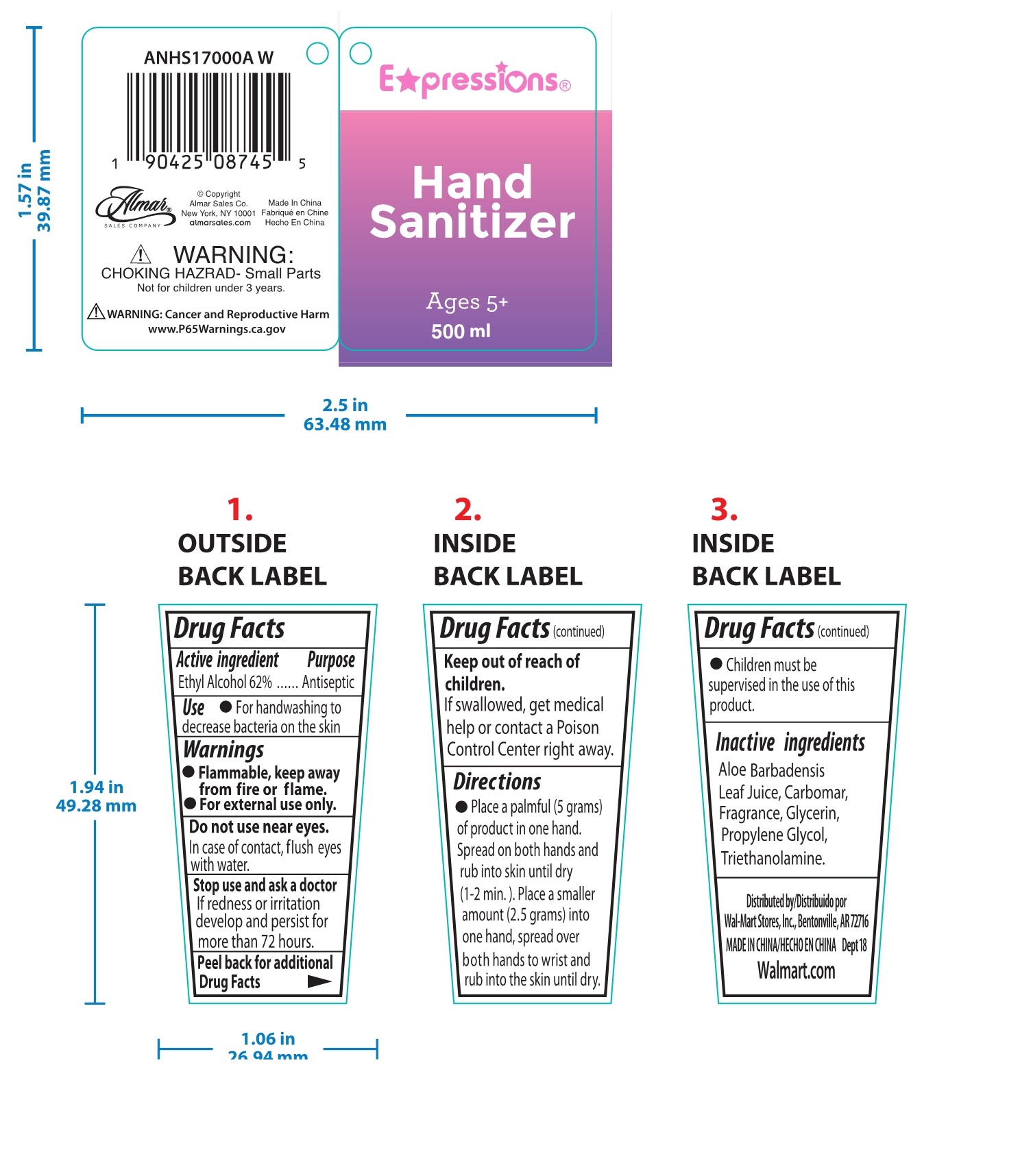 DRUG LABEL: Hand sanitizer
NDC: 74862-008 | Form: GEL
Manufacturer: Yiwu Shining Cosmetics Co.,Ltd
Category: otc | Type: HUMAN OTC DRUG LABEL
Date: 20210120

ACTIVE INGREDIENTS: ALCOHOL 62 mL/100 mL
INACTIVE INGREDIENTS: WATER; CARBOMER HOMOPOLYMER, UNSPECIFIED TYPE; GLYCERIN; SODIUM BICARBONATE; DENATONIUM BENZOATE

74862-008
Hand sanitizer gel

Active ingredient Purpose

Ethyl Alcohol 62%

PURPOSE

Antiseptic

INDICATIONS AND USAGE

For handwashing to decrease bacteria on the skin

WARNINGS

Flammable, keep away from fire or flame.
For external use only.

Do not use near eyes.
In case of contact, flush eyes with water.

Stop use and ask a doctor
If redness or irritation develop and persist for more than 72 hours.

Keep out of reach of children.
If swallowed, get medical help or contact a Poison Control Center right away.

Do not use near eyes.
In case of contact, flush eyes with water.

Do not use near eyes.
In case of contact, flush eyes with water.

Stop use and ask a doctor
If redness or irritation develop and persist for more than 72 hours.

Keep out of reach of children.
If swallowed, get medical help or contact a Poison Control Center right away.

Stop use and ask a doctor
If redness or irritation develop and persist for more than 72 hours.

Keep out of reach of children.
If swallowed, get medical help or contact a Poison Control Center right away.

DOSAGE AND ADMINISTRATION

Place a palmful (5 grams) of product in one hand.
Spread on both hands and rub into skin until dry (1-2 min.).
Place a smaller amount (2.5 grams) into one hand, spread overboth hands to wrist and rub into the skin until dry.
Children must be supervised in the use of this product

STORAGE AND HANDLING

/

Inactive ingredients

Aloe Barbadensis Leaf Juice, Carbomar, Fragrance, Glycerin, Propylene Glycol, Triethanolamine.

PACKAGE LABEL

74862-008-01 29ml

74862-008-02 30ml

74862-008-03 59ml

74862-008-04 60ml

74862-008-05 100ml

74862-008-06 120ml

74862-008-07 180ml

74862-008-08 240ml

74862-008-09 300ml

74862-008-10 500ml